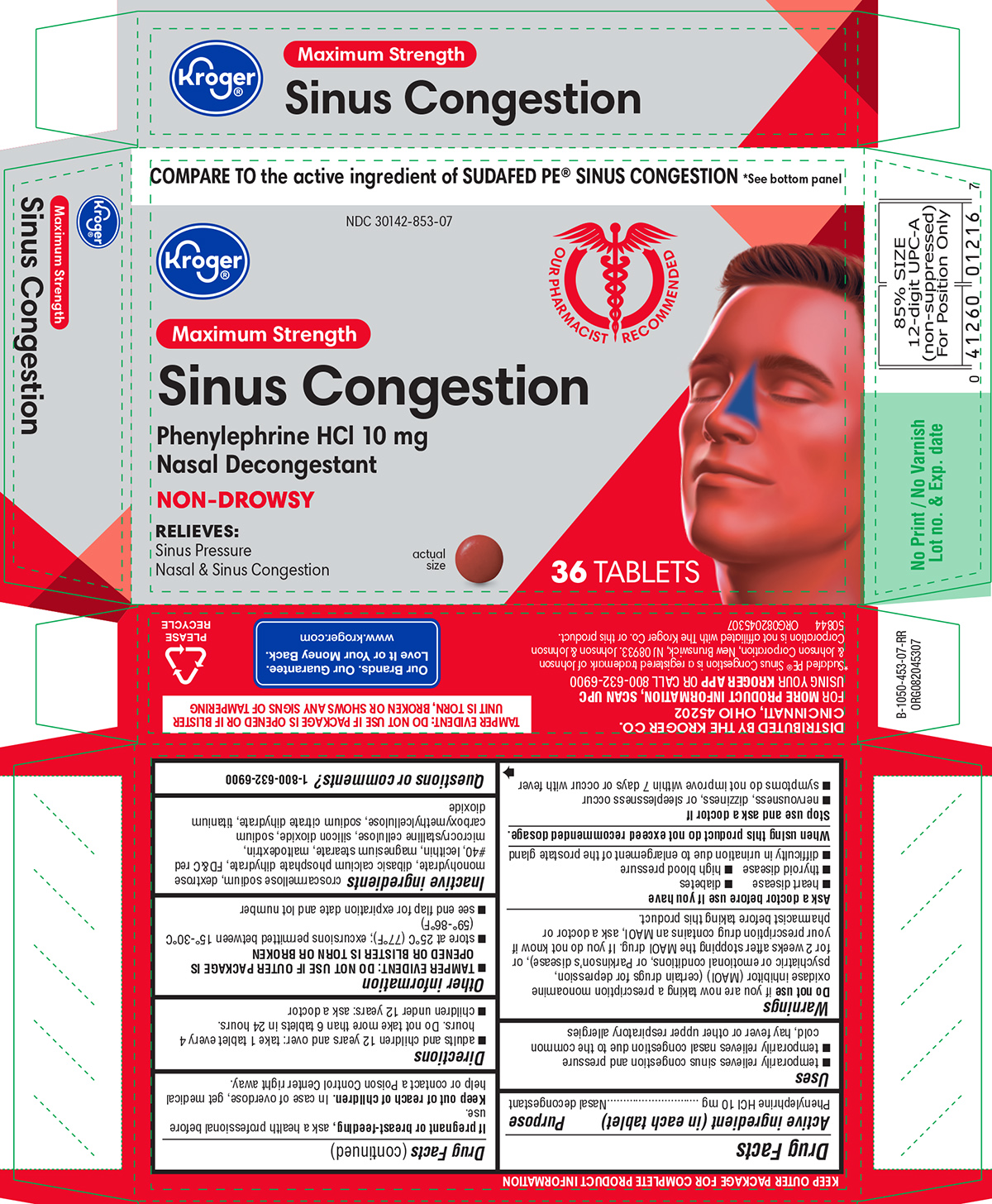 DRUG LABEL: Sinus Congestion
NDC: 30142-853 | Form: TABLET, FILM COATED
Manufacturer: Kroger Company
Category: otc | Type: HUMAN OTC DRUG LABEL
Date: 20250307

ACTIVE INGREDIENTS: PHENYLEPHRINE HYDROCHLORIDE 10 mg/1 1
INACTIVE INGREDIENTS: CROSCARMELLOSE SODIUM; DEXTROSE MONOHYDRATE; DIBASIC CALCIUM PHOSPHATE DIHYDRATE; FD&C RED NO. 40; LECITHIN, SOYBEAN; MAGNESIUM STEARATE; MALTODEXTRIN; MICROCRYSTALLINE CELLULOSE; SILICON DIOXIDE; CARBOXYMETHYLCELLULOSE SODIUM, UNSPECIFIED; TRISODIUM CITRATE DIHYDRATE; TITANIUM DIOXIDE

Kroger 44-453-Sinus Congestion

Active ingredient (in each tablet)

Phenylephrine HCl 10 mg

Purpose

Nasal decongestant

Uses

- temporarily relieves sinus congestion and pressure
- temporarily relieves nasal congestion due to the common cold, hay fever or other upper respiratory allergies

Warnings

Do not use

if you are now taking a prescription monoamine oxidase inhibitor (MAOI) (certain drugs for depression, psychiatric or emotional conditions, or Parkinson’s disease), or for 2 weeks after stopping the MAOI drug. If you do not know if your prescription drug contains an MAOI, ask a doctor or pharmacist before taking this product.

Ask a doctor before use if you have

- heart disease
- diabetes
- thyroid disease
- high blood pressure
- difficulty in urination due to enlargement of the prostate gland

When using this product

do not exceed recommended dosage.

Stop use and ask a doctor if

- nervousness, dizziness, or sleeplessness occur
- symptoms do not improve within 7 days or occur with fever

If pregnant or breast-feeding,

ask a health professional before use.

Keep out of reach of children.

In case of overdose, get medical help or contact a Poison Control Center right away.

Directions

- adults and children 12 years and over: take 1 tablet every 4 hours. Do not take more than 6 tablets in 24 hours.
- children under 12 years: ask a doctor

Other information

- TAMPER EVIDENT: DO NOT USE IF OUTER PACKAGE IS OPENED OR BLISTER IS TORN OR BROKEN
- store at 25°C (77°F); excursions permitted between 15°-30°C (59°-86°F)
- see end flap for expiration date and lot number

Inactive ingredients

croscarmellose sodium, dextrose monohydrate, dibasic calcium phosphate dihydrate, FD&C red #40, lecithin, magnesium stearate, maltodextrin, microcrystalline cellulose, silicon dioxide, sodium carboxymethylcellulose, sodium citrate dihydrate, titanium dioxide

Questions or comments?

1-800-632-6900

Principal display panel

Kroger®

COMPARE TO the active ingredient of SUDAFED PE® CONGESTION *See bottom panel

NDC 30142-853-07

Maximum Strength

Sinus Congestion
Phenylephrine HCl 10 mg
Nasal Decongestant

NON-DROWSY

RELIEVES:
• Sinus Pressure
• Nasal & Sinus Congestion

actual size

36 TABLETS

Our Pharmacists Recommended

TAMPER EVIDENT: DO NOT USE IF PACKAGE IS OPENED OR IF BLISTER
UNIT IS TORN, BROKEN OR SHOWS ANY SIGNS OF TAMPERING

Our Brands. Our Guarantee.
Love it or Your Money Back.
www.kroger.com

DISTRIBUTED BY THE KROGER CO.
CINCINNATI, OHIO 45202

FOR MORE PRODUCT INFORMATION, SCAN UPC
USING YOUR KROGER APP OR CALL 800-632-6900

*Sudafed PE® Sinus Congestion is a registered trademark of Johnson
& Johnson Corporation, New Brunswick, NJ 08933. Johnson & Johnson
Corporation is not affiliated with the Kroger Co. or this product.

50844 ORG082045307

Kroger 44-453